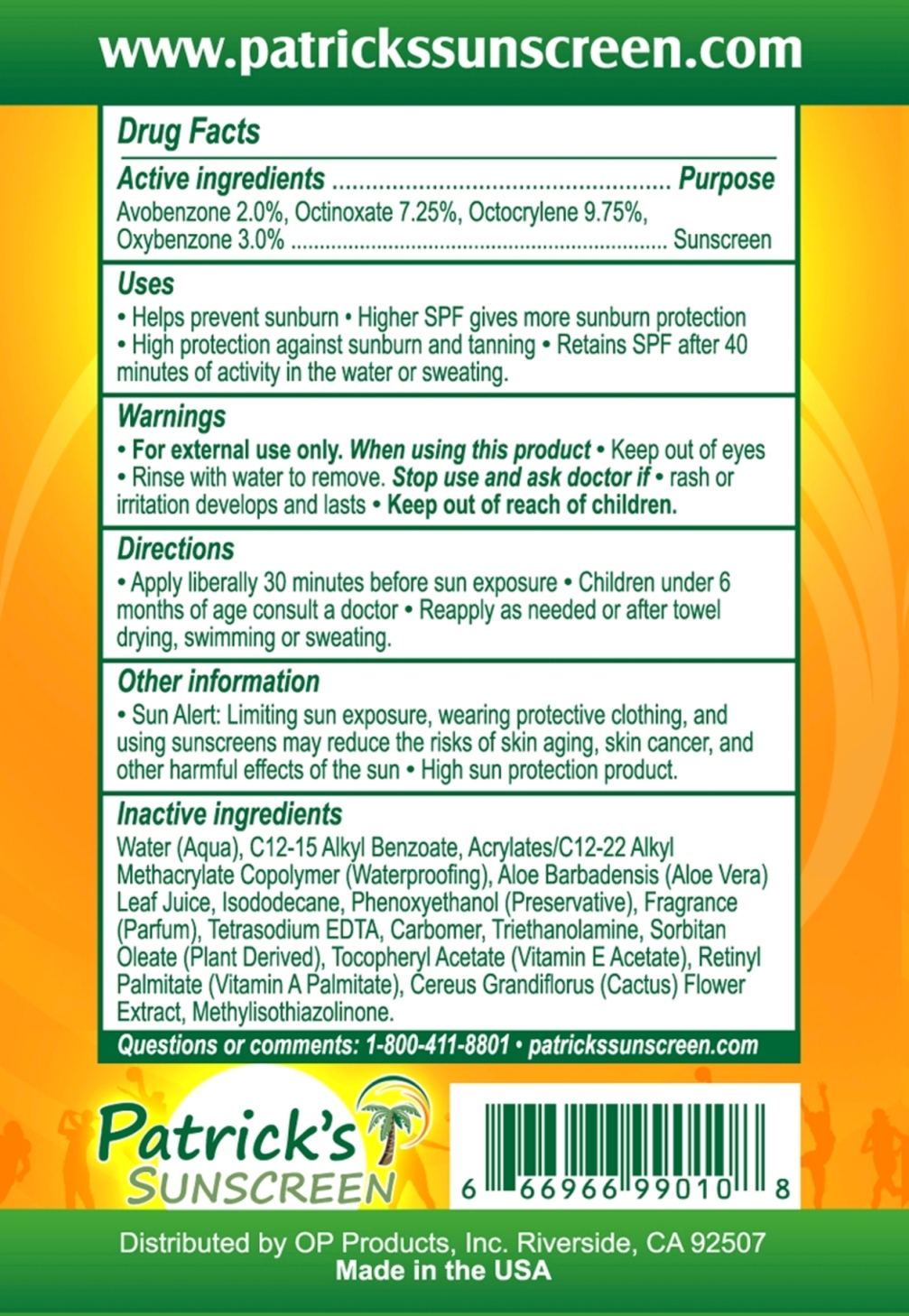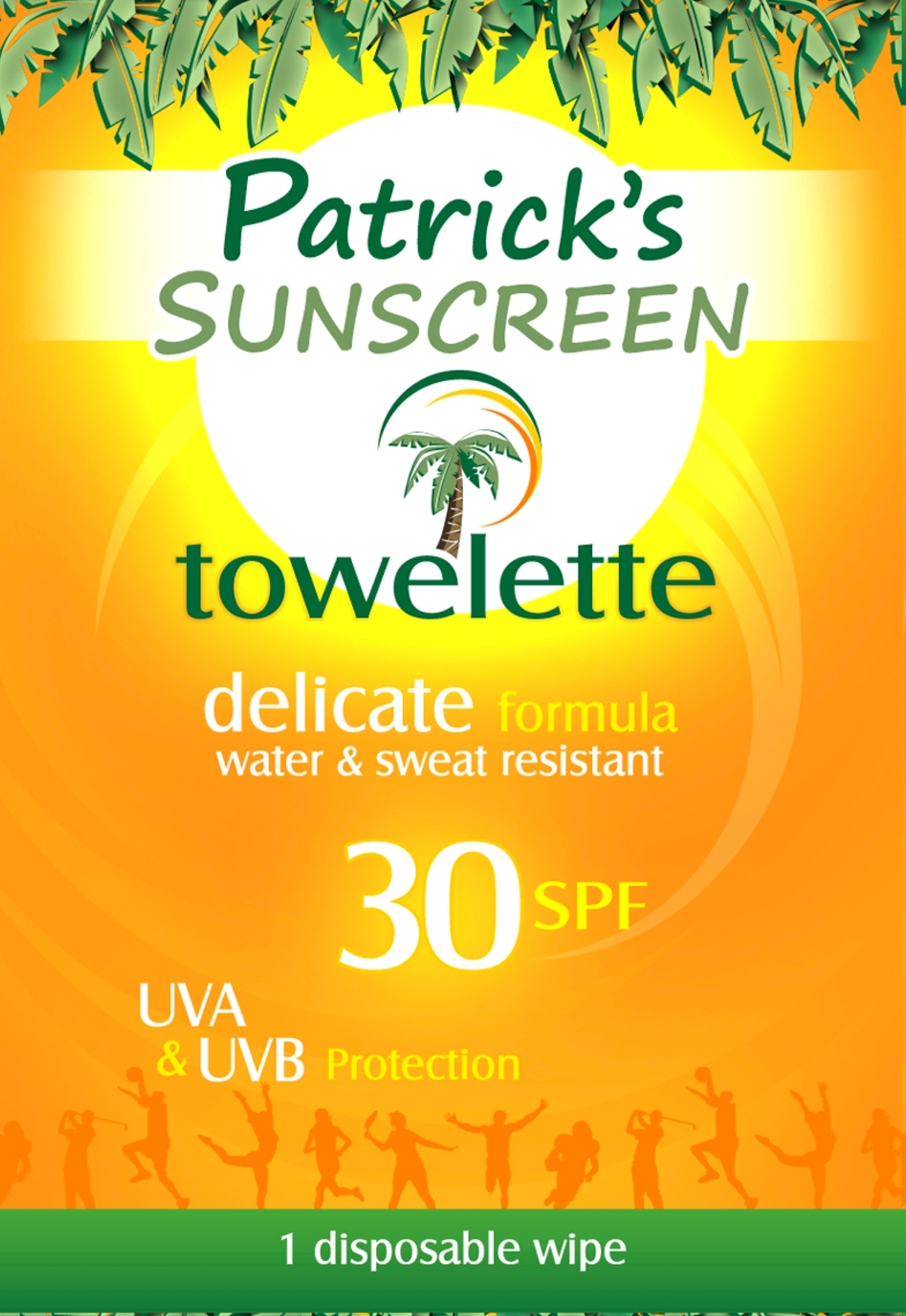 DRUG LABEL: Patricks Sunscreen
NDC: 40061-990 | Form: LOTION
Manufacturer: O.P. Products, Inc.
Category: otc | Type: HUMAN OTC DRUG LABEL
Date: 20120116

ACTIVE INGREDIENTS: Avobenzone 2 g/100 g; Octinoxate 7.25 g/100 g; Octocrylene 9.75 g/100 g; Oxybenzone 3 g/100 g
INACTIVE INGREDIENTS: Water; Alkyl (C12-15) Benzoate; Aloe Vera Leaf; Isododecane; Phenoxyethanol; Edetate Sodium; Carbomer Copolymer Type A; Trolamine; Sorbitan Monooleate; Alpha-Tocopherol Acetate; Vitamin A Palmitate; Selenicereus Grandiflorus Flower

Active ingredients.............

Avobenzone 2.0%, Octinoxate 7.25%, Octocrylene 9.75%, Oxybenzone 3.0%

Uses

- Helps prevent sunburn
- Higher SPF gives more sunburn protection
- High protection against sunburn and tanning
- Retains SPF after 40 minutes of activity in the water or sweating

Warnings

- For external use only. When using this product
- Keep out of eyes
- Rinse with warm water to remove. Stop use and ask doctor if
- rash or irritation develops and lasts

Directions

- Apply liberally 30 minutes before sun exposure
- Children under 6 months of age consult a doctor
- Reapply as needed or after towel drying, swimming or sweating

Purpose

Purpose...............Sunscreen

- Keep out of reach of children.

Inactive ingredients

Water (Aqua), C12-15 Alkyl Benzoate, Acrylates/C12-22 Alkyl Methacrylate Copolymer (Waterproofing), Aloe Barbadensis (Aloe Vera) Leaf Juice, Isododecane, Phenoxyethanol (Preservative), Fragrance (Parfum), Tetrasodium EDTA, Carbomer, Triethanolamine, Sorbitan Oleate (Plant Derived), Tocopheryl Acetate (Vitamin E Acetate), Retinyl Palmitate (Vitamin A Palmitate), Cereus Grandiflorus (Cactus) Flower Extract, Methylisothiazolinone.
Questions or comments: 1-800-411-8801 . patrickssunscreen.com

PACKAGE LABEL

Place holder text.